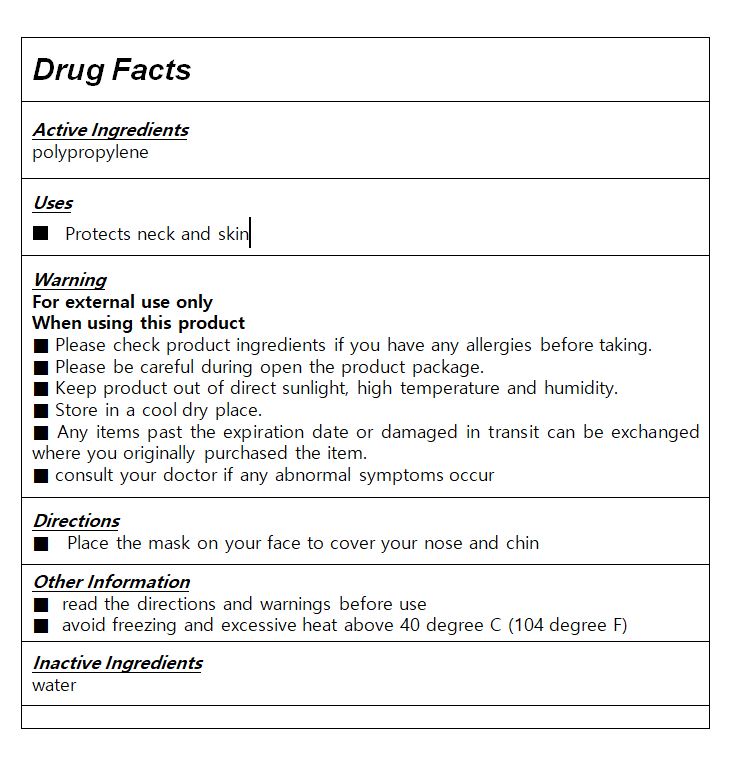 DRUG LABEL: FRESH CLEAN MASK
NDC: 81605-0001 | Form: CLOTH
Manufacturer: SG Sports Co.
Category: otc | Type: HUMAN OTC DRUG LABEL
Date: 20210304

ACTIVE INGREDIENTS: POLYPROPYLENE (30000 MW) 99 g/100 g
INACTIVE INGREDIENTS: WATER

Drug Facts

ACTIVE INGREDIENT

polypropylene

INACTIVE INGREDIENT

water

PURPOSE

Protects neck and skin from dry air for deep sleep

keep out of reach of the children

INDICATIONS AND USAGE

Place the mask on your face to cover your nose and chin

WARNINGS

1. For external use only.

1) Do not use over the wound and irritated skin with eczema or infections

2) Store in a cool and dry place, away from direct sun light

DOSAGE AND ADMINISTRATION

for external use only